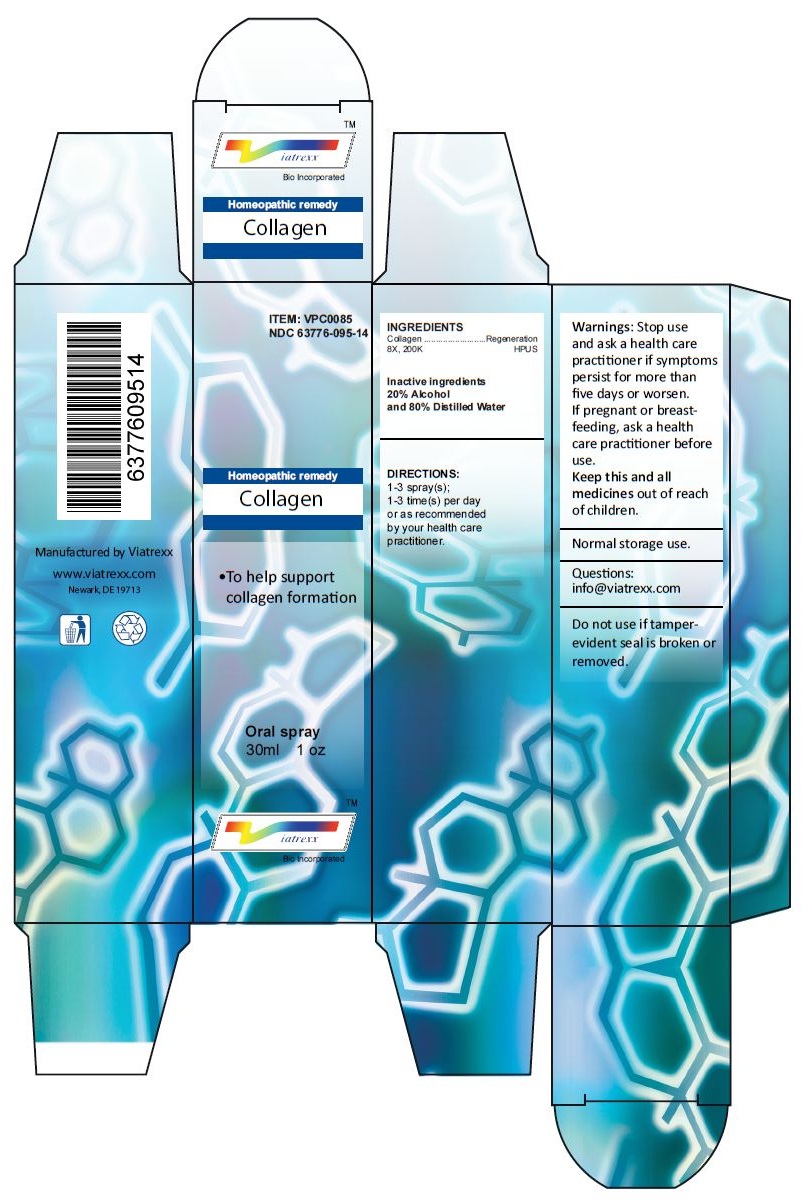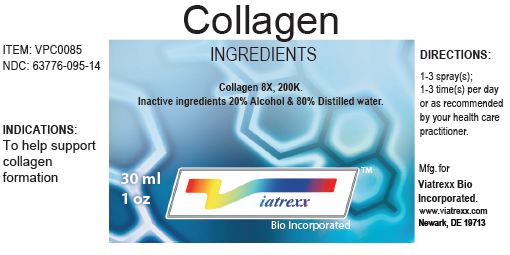 DRUG LABEL: Collagen
NDC: 63776-095 | Form: SPRAY
Manufacturer: VIATREXX BIO INCORPORATED
Category: homeopathic | Type: HUMAN OTC DRUG LABEL
Date: 20230110

ACTIVE INGREDIENTS: PORK COLLAGEN 200 [kp_C]/1 mL
INACTIVE INGREDIENTS: ALCOHOL; WATER

Collagen

Active Ingredients

Collagen 8X, 200K

Purpose:

Collagen | Regeneration

Uses

To help support collagen formation

Warnings

Stop use and ask a health care practitioner if symptoms persist for more than five days or worsen. If pregnant or breastfeeding, ask a health care practitioner before use.

Dosage

1-3 spray(s); 1-3 time(s) per day or as recommended by your health care practitioner.

KEEP OUT OF REACH OF CHILDREN

Keep this and all medicines out of reach of children.

Other Ingredients

20% Alcohol and 80% Water

Other Information

Normal storage use.
Do not use if tamper-evident seal is broken or removed.

Questions

info@viatrexx.com

Principal Display Panel

ITEM: VPC0085
NDC 63776-095-14
Homeopathic remedy
Collagen
• To help support collagen formation
Oral spray
30ml 1 oz
Viatrexx™ Bio Incorporated
Manufactured by Viatrexx
www.viatrexx.com
Newark, DE 19713

Collagen
30 ml
1 oz
Viatrexx™ Bio Incorporated
ITEM: VPC0085
NDC: 63776-095-14
INDICATIONS:
To help support collagen formation
DIRECTIONS:
1-3 spray(s); 1-3 time(s) per day or as recommended by your health care practitioner.
Mfg. for
Viatrexx Bio Incorporated.
www.viatrexx.com
Newark, DE 19713